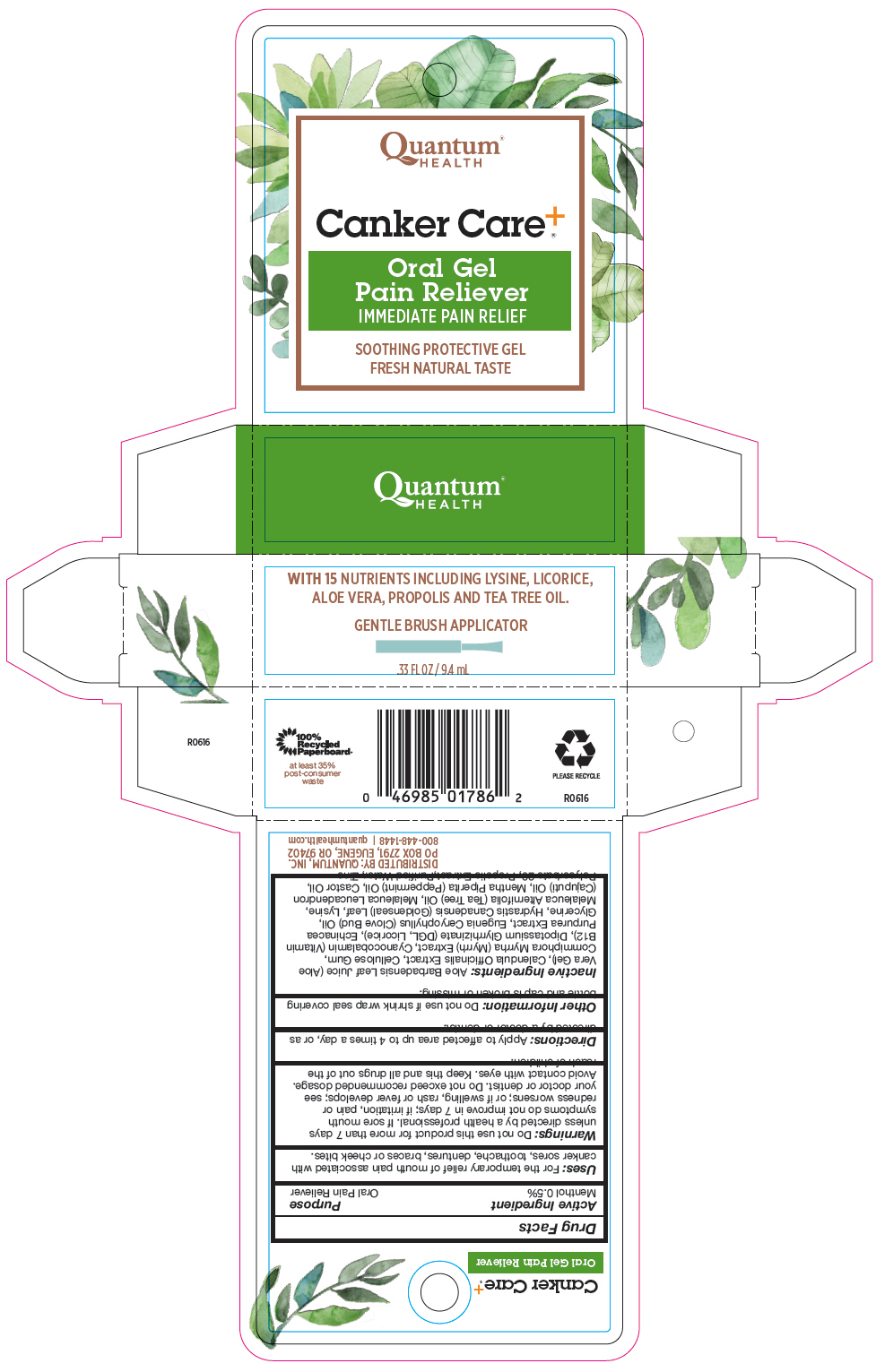 DRUG LABEL: Canker Care Plus
NDC: 70084-500 | Form: LIQUID
Manufacturer: Quantum, Inc.
Category: otc | Type: HUMAN OTC DRUG LABEL
Date: 20251020

ACTIVE INGREDIENTS: MENTHOL, UNSPECIFIED FORM 5 mg/1 mL
INACTIVE INGREDIENTS: ECHINACEA PURPUREA WHOLE; TEA TREE OIL; MELALEUCA CAJUPUTI LEAF OIL; GOLDENSEAL; LYSINE HYDROCHLORIDE; PROPOLIS WAX; WATER; CASTOR OIL; CYANOCOBALAMIN; ZINC GLUCONATE; CARBOXYMETHYLCELLULOSE SODIUM, UNSPECIFIED; MYRRH; GLYCYRRHIZINATE DIPOTASSIUM; CLOVE OIL; GLYCERIN; LICORICE; PEPPERMINT OIL; POLYSORBATE 20; CALENDULA OFFICINALIS FLOWER

Canker Care^+®

Drug Facts

Active Ingredient

Menthol 0.5%

Purpose

Oral Pain Reliever

Uses

For the temporary relief of mouth pain associated with canker sores, toothache, dentures, braces or cheek bites.

Warnings

Do not use this product for more than 7 days unless directed by a health professional. If sore mouth symptoms do not improve in 7 days; if irritation, pain or redness worsens; or if swelling, rash or fever develops; see your doctor or dentist. Do not exceed recommended dosage. Avoid contact with eyes.

KEEP OUT OF REACH OF CHILDREN

Keep this and all drugs out of the reach of children.

Directions

Apply to affected area up to 4 times a day, or as directed by a doctor or dentist.

Other Information

Do not use if shrink wrap seal covering bottle and cap is broken or missing.

Inactive Ingredients

Aloe Barbadensis Leaf Juice (Aloe Vera Gel), Calendula Officinalis Extract, Cellulose Gum, Commiphora Myrrha (Myrrh) Extract, Cyanocobalamin (Vitamin B12), Dipotassium Glyrrhizinate (DGL, Licorice), Echinacea Purpurea Extract, Eugenia Ceryophyllus (Clove Bud) Oil, Glycerine, Hydrastis Canadensis (Goldenseal) Leaf, Lysine, Melaleuca Alternifolia (Tea Tree) Oil, Melaleuca Leucadendron (Cajuputi) Oil, Mentha Piperita (Peppermint) Oil, Castor Oil, Polysorbate 20, Propolis Extract,Purified Water, Zinc

DISTRIBUTED BY: QUANTUM, INC.
PO BOX 2791, EUGENE, OR 97402

PRINCIPAL DISPLAY PANEL - 9.4 mL Bottle Carton

Quantum®
HEALTH

Canker Care^+®

Oral Gel
Pain Reliever
IMMEDIATE PAIN RELIEF

SOOTHING PROTECTIVE GEL
FRESH NATURAL TASTE

WITH 15NUTRIENTS INCLUDING LYSINE, LICORICE,
ALOE VERA, PROPOLIS AND TEA TREE OIL.

GENTLE BRUSH APPLICATOR

.33 FL OZ / 9.4 mL